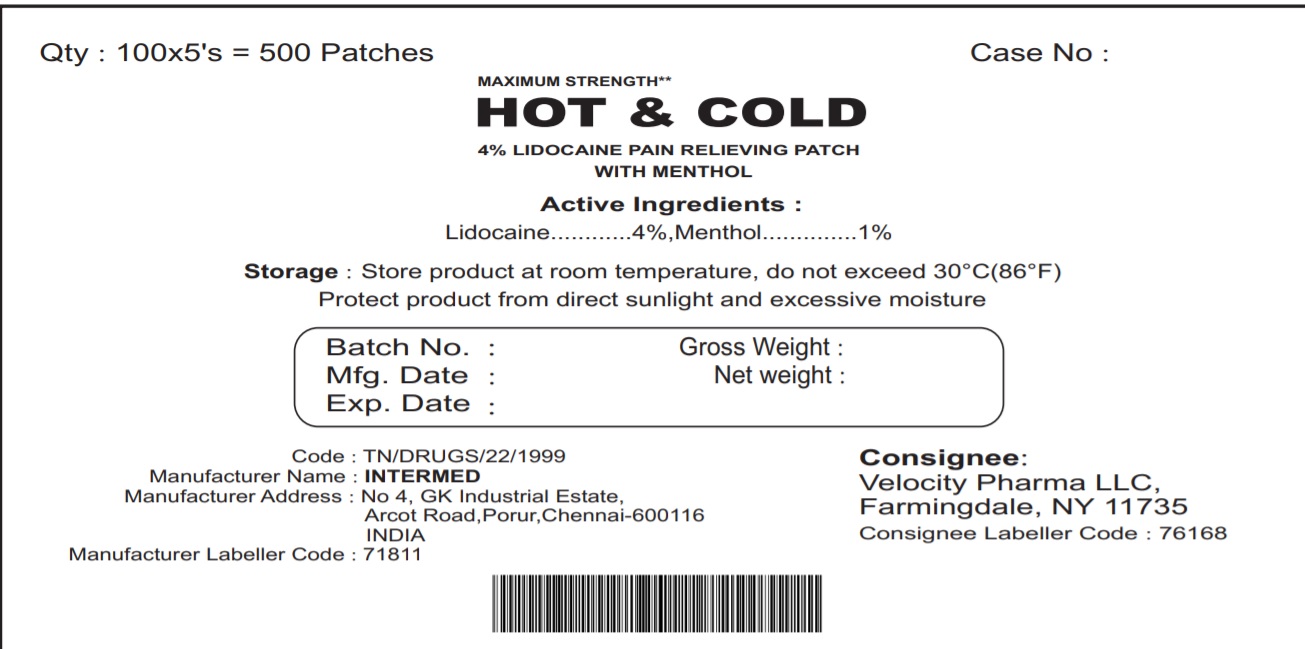 DRUG LABEL: Hot and Cold Lidocaine with Menthol Patch
NDC: 71811-002 | Form: PATCH
Manufacturer: InterMed Laboratories Private Limited
Category: otc | Type: HUMAN OTC DRUG LABEL
Date: 20250301

ACTIVE INGREDIENTS: LIDOCAINE 240 mg/1 1; MENTHOL 60 mg/1 1
INACTIVE INGREDIENTS: DIHYDROXYALUMINUM AMINOACETATE; EDETATE DISODIUM ANHYDROUS; GLYCERIN; METHYLPARABEN; POLYVINYL ALCOHOL, UNSPECIFIED; PROPYLPARABEN; WATER; CARBOXYMETHYLCELLULOSE SODIUM, UNSPECIFIED FORM; SODIUM POLYACRYLATE (2500000 MW); TARTARIC ACID; TITANIUM DIOXIDE

Hot and Cold Lidocaine with Menthol Patch- Bulk

Drug Facts

ACTIVE INGREDIENT

Active Ingredients | Purpose
Lidocaine 4 % (240 mg) | Topical analgesic
Menthol 1% (60 mg) | Topical analgesic

Uses

Temporarily relieves minor pain associated with: arthritis, simple backache, bursitis, tendonitis, muscle strains, sprains & bruises.

Warnings

For external use only.

Do not use if you are allergic or sensitive to lidocaine or menthol. Do not use if pouch is damaged or opened.

When using this product

- use only as directed
- avoid contact with eyes or mucous membranes
- do not apply to open wounds or sensitive skin
- do not bandage tightly or use a heating pad

Stop use and ask a doctor if

- excessive redness or irritation is present
- condition worsens
- pain persists for more than 7 days
- symptoms clear up and occur again within a few days

PREGNANCY OR BREAST FEEDING

If pregnant or breast-feeding, ask a health professional before use.

Keep out of Reach of children. If swallowed, get medical help or contact a Poison control Center right away.

Directions

- adults: apply patch to affected area for a maximum of 12 hours. Do not use more than 1 patch every 24 hours.
- children: consult your physician
- remove protective film, gently apply to affected area.

Inactive Ingredients

Dihydroxyaluminium aminoacetate, disodium EDTA, glycerin, methylparaben, polyvinyl alcohol, propyl
paraben, propylene glycol, purified water, sodium carboxymethyl cellulose, sodium polyacrylate, tartaric
acid, titanium dioxide